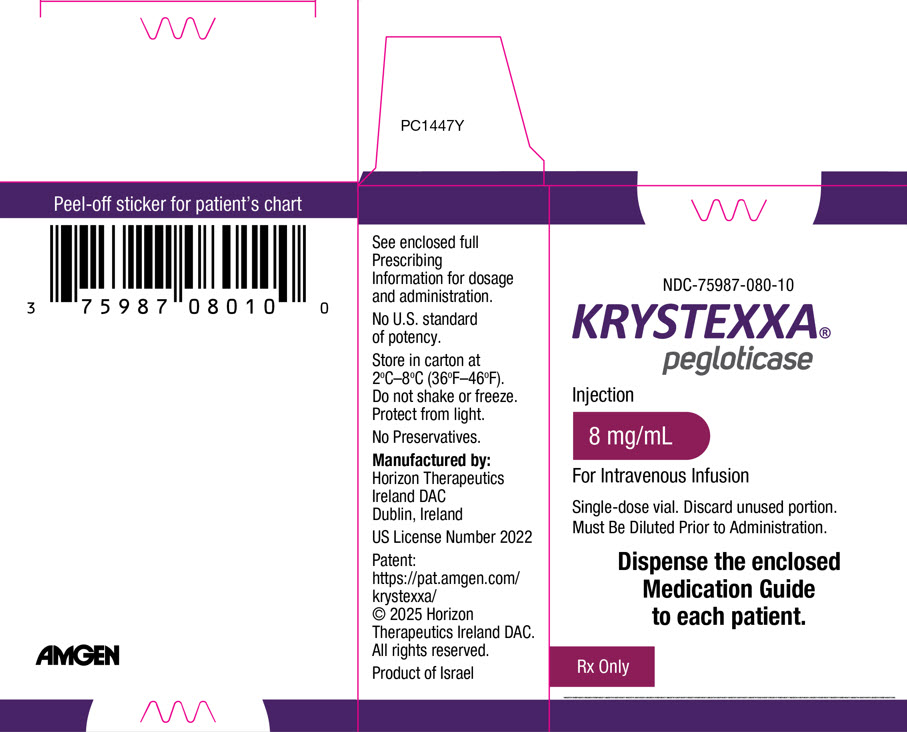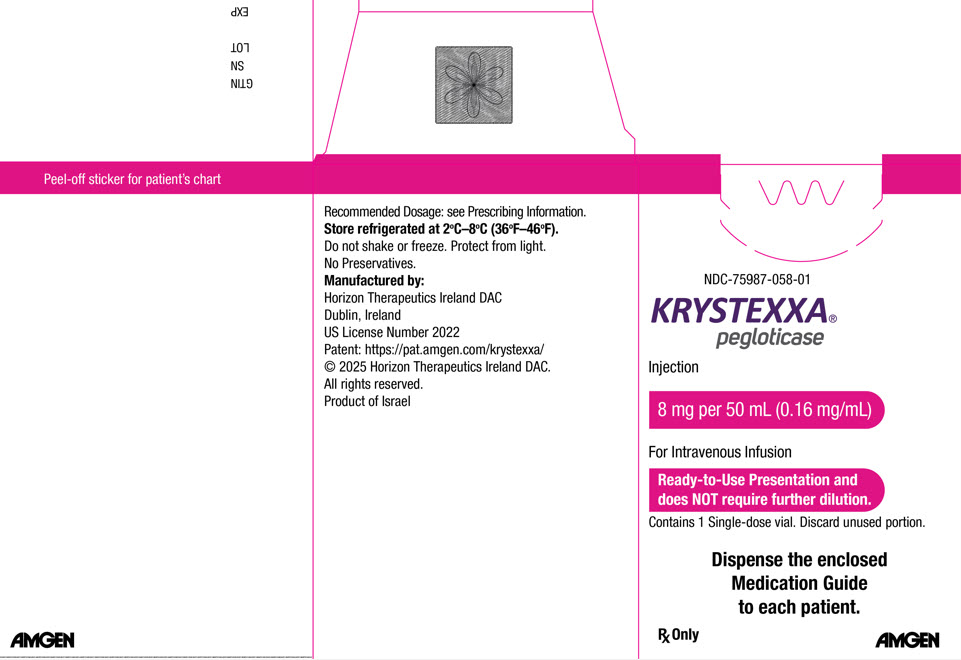 DRUG LABEL: Krystexxa
NDC: 75987-080 | Form: INJECTION, SOLUTION
Manufacturer: Horizon Therapeutics USA, Inc.
Category: prescription | Type: HUMAN PRESCRIPTION DRUG LABEL
Date: 20250829

ACTIVE INGREDIENTS: PEGLOTICASE 8 mg/1 mL
INACTIVE INGREDIENTS: SODIUM PHOSPHATE, DIBASIC, DIHYDRATE; SODIUM CHLORIDE; SODIUM PHOSPHATE, MONOBASIC, DIHYDRATE; WATER

HIGHLIGHTS OF PRESCRIBING INFORMATION

These highlights do not include all the information needed to use KRYSTEXXA safely and effectively. See full prescribing information for KRYSTEXXA.
KRYSTEXXA® (pegloticase) injection, for intravenous use
Initial U.S. Approval: 2010

WARNING: ANAPHYLAXIS and INFUSION REACTIONS, G6PD DEFICIENCY ASSOCIATED HEMOLYSIS and METHEMOGLOBINEMIA

See full prescribing information for complete boxed warning.

- Anaphylaxis and infusion reactions have been reported to occur during and after administration of KRYSTEXXA. (5.1, 5.2)
- Anaphylaxis may occur with any infusion, including a first infusion, and generally manifest within 2 hours of the infusion. However, delayed hypersensitivity reactions have also been reported. (5.1)
- KRYSTEXXA should be administered in healthcare settings and by healthcare providers prepared to manage anaphylaxis and infusion reactions. (5.1, 5.2)
- Pre-medicate with antihistamines and corticosteroids and closely monitor for anaphylaxis for an appropriate period of time after administration of KRYSTEXXA. (5.1, 5.2)
- Monitor serum uric acid levels prior to each infusion and discontinue treatment if levels increase to above 6 mg/dL, particularly when 2 consecutive levels above 6 mg/dL are observed. (5.2)
- Screen patients at risk for G6PD deficiency prior to starting KRYSTEXXA. Hemolysis and methemoglobinemia have been reported with KRYSTEXXA in patients with G6PD deficiency. KRYSTEXXA is contraindicated in patients with G6PD deficiency. (4, 5.3)

RECENT MAJOR CHANGES

Dosage and Administration (2.1, 2.3) | 8/2025

1 INDICATIONS AND USAGE

KRYSTEXXA® (pegloticase) is a PEGylated uric acid specific enzyme indicated for the treatment of chronic gout in adult patients refractory to conventional therapy. (1)

Limitations of Use:
KRYSTEXXA is not recommended for the treatment of asymptomatic hyperuricemia. (1)

2 DOSAGE AND ADMINISTRATION

Recommended Dosage

- The recommended dosage is KRYSTEXXA 8 mg every two weeks given as an intravenous infusion, co-administered with weekly methotrexate 15 mg orally. KRYSTEXXA alone may be used in patients for whom methotrexate is contraindicated or not clinically appropriate. (2.2)
- Methotrexate with folic acid or folinic acid supplementation should be initiated at least 4 weeks prior to initiating, and throughout treatment with KRYSTEXXA. (2.2)
- Discontinue oral urate-lowering agents before starting KRYSTEXXA. (2.1)
- Monitor serum uric acid levels before each infusion. (2.1)
- Pre-medicate patients with antihistamines and corticosteroids. (2.1, 5.1, 5.2)

Preparation and Administration

- Do not administer as an intravenous push or bolus. (2.1)
- KRYSTEXXA injection is supplied as a Ready-to-Use (with hanger label) single-dose vial or a To-be-Diluted single-dose vial. (2.3)
- See full prescribing information for information on preparation and administration for each vial presentation. (2.1, 2.2, 2.3)

3 DOSAGE FORMS AND STRENGTHS

- Injection: Ready-to-Use 8 mg/50 mL (0.16 mg/mL) in a single-dose vial (3)
- Injection: To-be-Diluted 8 mg/mL in a single-dose vial (3)

4 CONTRAINDICATIONS

- Patients with glucose-6-phosphate dehydrogenase (G6PD) deficiency. (4)
- Patients with history of serious hypersensitivity reactions, including anaphylaxis, to KRYSTEXXA or any of its components. (4)

5 WARNINGS AND PRECAUTIONS

- Anaphylaxis: Anaphylaxis may occur with any KRYSTEXXA infusion. Pre-medicate and monitor patients. (5.1)
- Infusion Reactions: Infusion reactions occurred in patients treated with KRYSTEXXA. Pre-medicate and monitor patients. (5.2)
- G6PD Deficiency Associated Hemolysis and Methemoglobinemia: Screen patients at risk for G6PD deficiency. Do not administer KRYSTEXXA to patients with G6PD deficiency. (5.3)
- Gout Flares: Gout flare prophylaxis is recommended for at least the first 6 months of KRYSTEXXA therapy. (5.4)
- Congestive Heart Failure: Congestive heart failure exacerbation may occur. Monitor patients closely following infusion. (5.5)

6 ADVERSE REACTIONS

- Co-administration with methotrexate: The most common adverse reactions (≥5% of patients) are gout flares, arthralgia, COVID-19, nausea and fatigue. (6.1)
- KRYSTEXXA alone: The most common adverse reactions (≥5% of patients) are gout flares, infusion reactions, nausea, contusion or ecchymosis, nasopharyngitis, constipation, chest pain, anaphylaxis and vomiting. (6.1)

To report SUSPECTED ADVERSE REACTIONS, contact Amgen Inc. at 1-800-77-AMGEN (1-800-772-6436) or FDA at 1-800-FDA-1088 or www.fda.gov/medwatch.

FULL PRESCRIBING INFORMATION

WARNING: ANAPHYLAXIS and INFUSION REACTIONS, G6PD DEFICIENCY ASSOCIATED HEMOLYSIS and METHEMOGLOBINEMIA

- Anaphylaxis and infusion reactions have been reported to occur during and after administration of KRYSTEXXA. (5.1, 5.2)
- Anaphylaxis may occur with any infusion, and generally manifests within 2 hours of the infusion. However, delayed hypersensitivity reactions have also been reported. (5.1)
- KRYSTEXXA should be administered in healthcare settings and by healthcare providers prepared to manage anaphylaxis and infusion reactions. (5.1, 5.2)
- Premedicate with antihistamines and corticosteroids and closely monitor for anaphylaxis for an appropriate period of time after administration of KRYSTEXXA. (5.1, 5.2)
- Monitor serum uric acid levels prior to each infusion and discontinue treatment if levels increase to above 6 mg/dL, particularly when 2 consecutive levels above 6 mg/dL are observed. (5.2)
- Screen patients at risk for G6PD deficiency prior to starting KRYSTEXXA. Hemolysis and methemoglobinemia have been reported with KRYSTEXXA in patients with G6PD deficiency. KRYSTEXXA is contraindicated in patients with G6PD deficiency. (4, 5.3)

1 INDICATIONS AND USAGE

KRYSTEXXA® (pegloticase) is indicated, for the treatment of chronic gout in adult patients refractory to conventional therapy.

Gout refractory to conventional therapy occurs in patients who have failed to normalize serum uric acid and whose signs and symptoms are inadequately controlled with xanthine oxidase inhibitors at the maximum medically appropriate dose or for whom these drugs are contraindicated.

Limitations of Use:

KRYSTEXXA is not recommended for the treatment of asymptomatic hyperuricemia.

2 DOSAGE AND ADMINISTRATION

2.1 Important Administration Instructions

Precautions Prior to Treatment

It is recommended that before starting KRYSTEXXA patients discontinue oral urate-lowering medications and not institute therapy with oral urate-lowering agents while patients are on KRYSTEXXA therapy.

Monitoring Therapy: The risk of infusion reactions, including anaphylaxis, is higher in patients who have lost therapeutic response. Monitor serum uric acid levels prior to each infusion and discontinue treatment if levels increase to above 6 mg/dL, particularly when 2 consecutive levels above 6 mg/dL are observed [see Warnings and Precautions (5.1, 5.2)].

Infusion Reaction Precautions

KRYSTEXXA should be administered in a healthcare setting by healthcare providers prepared to manage infusion reactions, including anaphylaxis. Observe patients for an appropriate period of time after administration [see Warnings and Precautions (5.1, 5.2)].

Patients should receive pre-infusion medications (e.g., antihistamines, corticosteroids), to minimize the risk of infusion reactions, including anaphylaxis.

If an infusion reaction occurs during the administration of KRYSTEXXA, the infusion may be slowed, or stopped and restarted at a slower rate, at the discretion of the physician. Since infusion reactions can occur after completion of infusion, observation of patients for approximately an hour post-infusion should be considered [see Warnings and Precautions (5.2), Adverse Reactions (6.1)].

Administration Precautions

Do not administer KRYSTEXXA as an intravenous push or bolus. KRYSTEXXA should only be administered by intravenous infusion. An infusion pump may be used for the Ready-to-Use vial. Gravity feed, syringe-type pump, or infusion pump may be used for the To-Be-Diluted vial [see Dosage and Administration (2.3)].

2.2 Recommended Dosage and Administration

The recommended dosage is KRYSTEXXA 8 mg given as an intravenous infusion every two weeks, co-administered with weekly oral methotrexate 15 mg and folic acid or folinic acid supplementation. KRYSTEXXA alone may be used in patients for whom methotrexate is contraindicated or not clinically appropriate.

If co-administering with methotrexate, start weekly methotrexate and folic acid or folinic acid supplementation at least 4 weeks prior to initiating, and throughout treatment with KRYSTEXXA [see Clinical Studies (14)]. Refer to the Full Prescribing Information for methotrexate.

The optimal treatment duration with KRYSTEXXA has not been established.

2.3 Preparation and Administration Instructions

KRYSTEXXA injection is supplied as either a Ready-to-Use single-dose vial (with hanger label) or a To-be-Diluted single-dose vial.

Ready-to-Use KRYSTEXXA 8 mg/50 mL (0.16 mg/mL) single-dose vial (with hanger label)

Step 1: Parenteral drug products should be inspected visually for particulate matter and discoloration prior to administration, whenever solution and container permit. Do not use vial if either is present.

Step 2: Allow the Ready-to-Use vial to reach room temperature at 20°C to 25°C (68°F to 77°F). KRYSTEXXA in a vial should never be subjected to artificial heating (e.g., hot water, microwave). Unopened vial may be stored for up to 4 hours at room temperature.

Step 3: Use appropriate aseptic technique. Insert a vented intravenous set through the septum of the vial. Once the stopper is punctured, use immediately.

Step 4: To administer, invert and hang the vial utilizing the built-in hanger label affixed to the bottom of the vial.

Step 5: Administer as an intravenous infusion over a period of no less than 120 minutes using an infusion pump. After the entire contents of the vial have been administered, flush the injection line with Sodium Chloride Injection to ensure delivery of the required dose.

To-be-Diluted KRYSTEXXA 8 mg/mL single-dose vial

Step 1: Parenteral drug products should be inspected visually for particulate matter and discoloration prior to administration, whenever solution and container permit. Do not use vial if either is present.

Step 2: Use appropriate aseptic technique. Withdraw 1 mL of KRYSTEXXA (To-be-Diluted) from the vial into a sterile syringe. Discard any unused portion of product remaining in the vial. Inject into a single 250 mL bag of 0.9% Sodium Chloride Injection, USP or 0.45% Sodium Chloride Injection, USP for intravenous infusion. Do not mix or dilute with other drugs.

Step 3: Gently invert the infusion bag containing the dilute KRYSTEXXA solution a number of times to ensure thorough mixing. Do not shake.

Step 4: Before administration, allow the diluted solution of KRYSTEXXA to reach room temperature. KRYSTEXXA in a vial or in an intravenous infusion fluid should never be subjected to artificial heating (e.g., hot water, microwave).

KRYSTEXXA diluted in infusion bags is stable for 4 hours at 2°C to 8°C (36°F to 46°F) and at room temperature at 20°C to 25°C (68°F to 77°F). However, it is recommended that diluted solutions be stored under refrigeration, not frozen, protected from light, and used within 4 hours of dilution [see How Supplied/Storage and Handling (16)].

Step 5: Administer as an intravenous infusion over 120 minutes using gravity feed, syringe-type pump, or infusion pump.

3 DOSAGE FORMS AND STRENGTHS

KRYSTEXXA is a clear and colorless solution, containing 8 mg of pegloticase expressed as concentrations of uricase protein available as:

- Injection: Ready-to-Use 8 mg/50 mL (0.16 mg/mL) in a single-dose vial (with hanger label) [see Dosage and Administration (2.3)].
- Injection: To-be-Diluted 8 mg/mL in a single-dose vial [see Dosage and Administration (2.3)].

4 CONTRAINDICATIONS

KRYSTEXXA is contraindicated in:

- Patients with glucose-6-phosphate dehydrogenase (G6PD) deficiency [see Warnings and Precautions (5.3)].
- Patients with history of serious hypersensitivity reactions, including anaphylaxis, to KRYSTEXXA or any of its components.

5 WARNINGS AND PRECAUTIONS

5.1 Anaphylaxis

In a 52-week controlled trial, which evaluated KRYSTEXXA co-administered with methotrexate compared to KRYSTEXXA alone, subjects were pre-treated with standardized infusion reaction prophylaxis and were discontinued from treatment with KRYSTEXXA if serum uric acid levels increased to above 6 mg/dL at 2 consecutive visits after the initiation of KRYSTEXXA therapy to reduce the risk of anaphylaxis. One subject randomized to the group treated with KRYSTEXXA co-administered with methotrexate (1%) experienced anaphylaxis during the first infusion and no subjects experienced anaphylaxis in the group treated with KRYSTEXXA alone [see Adverse Reactions (6.1), Clinical Studies (14)].

During pre-marketing clinical trials with KRYSTEXXA alone, KRYSTEXXA was not discontinued following 2 consecutive serum uric acid levels above 6 mg/dL. Anaphylaxis was reported with a frequency of 6.5% (8/123) of subjects treated with KRYSTEXXA every 2 weeks and 4.8% (6/126) for the every 4-week dosing regimen. There were no cases of anaphylaxis in subjects receiving placebo. Anaphylaxis generally occurred within 2 hours after treatment.

Diagnostic criteria of anaphylaxis were skin or mucosal tissue involvement, and, either airway compromise, and/or reduced blood pressure with or without associated symptoms, and a temporal relationship to KRYSTEXXA or placebo injection with no other identifiable cause. Manifestations included wheezing, peri-oral or lingual edema, or hemodynamic instability, with or without rash or urticaria, nausea or vomiting. Cases occurred in patients being pre-treated with one or more doses of an oral antihistamine, an intravenous corticosteroid and/or acetaminophen. This pre-treatment may have blunted or obscured symptoms or signs of anaphylaxis and therefore the reported frequency may be an underestimate.

KRYSTEXXA should be administered in a healthcare setting by healthcare providers prepared to manage anaphylaxis. Patients should be pre-treated with antihistamines and corticosteroids. Anaphylaxis may occur with any infusion, including a first infusion, and generally manifests within 2 hours of the infusion. However, delayed type hypersensitivity reactions have also been reported. Patients should be closely monitored for an appropriate period of time for anaphylaxis after administration of KRYSTEXXA. Patients should be informed of the symptoms and signs of anaphylaxis and instructed to seek immediate medical care should anaphylaxis occur after discharge from the healthcare setting.

The risk of anaphylaxis is higher in patients whose uric acid level increases to above 6 mg/dL, particularly when 2 consecutive levels above 6 mg/dL are observed. Monitor serum uric acid levels prior to infusions and discontinue treatment if levels increase to above 6 mg/dL. Because of the possibility that concomitant use of oral urate-lowering therapy and KRYSTEXXA may potentially blunt the rise of serum uric acid levels, it is recommended that before starting KRYSTEXXA patients discontinue oral urate-lowering medications and not institute therapy with oral urate-lowering agents while taking KRYSTEXXA.

5.2 Infusion Reactions

In a 52-week, controlled trial which evaluated KRYSTEXXA co-administered with methotrexate compared to KRYSTEXXA alone [see Adverse Reactions (6.1), Clinical Studies (14)], subjects were pre-treated with standardized infusion reaction prophylaxis and were discontinued from treatment with KRYSTEXXA if serum uric acid levels increased to above 6 mg/dL at 2 consecutive visits after the initiation of KRYSTEXXA therapy to reduce the risk of infusion reactions. Infusion reactions were reported in 4% of subjects in the KRYSTEXXA co-administered with methotrexate group compared to 31% of subjects treated with KRYSTEXXA alone experienced infusion reactions [see Adverse Reactions (6.1), Clinical Studies (14)]. In both treatment groups, the majority of infusion reactions occurred at the first or second KRYSTEXXA infusion and during the time of infusion. Manifestations of these infusion reactions were similar to that observed in the pre-marketing trials.

During pre-marketing 24-week controlled clinical trials with KRYSTEXXA alone, KRYSTEXXA was not discontinued following 2 consecutive serum uric acid levels above 6 mg/dL. Infusion reactions were reported in 26% of subjects treated with KRYSTEXXA 8 mg every 2 weeks, and 41% of subjects treated with KRYSTEXXA 8 mg every 4 weeks, compared to 5% of subjects treated with placebo. These infusion reactions occurred in subjects being pre-treated with an oral antihistamine, intravenous corticosteroid and/or acetaminophen. This pre-treatment may have blunted or obscured symptoms or signs of infusion reactions and therefore the reported frequency may be an underestimate.

Manifestations of these reactions included urticaria (frequency of 10.6%), dyspnea (frequency of 7.1%), chest discomfort (frequency of 9.5%), chest pain (frequency of 9.5%), erythema (frequency of 9.5%), and pruritus (frequency of 9.5%). These manifestations overlap with the symptoms of anaphylaxis, but in a given patient did not occur together to satisfy the clinical criteria for diagnosing anaphylaxis. Infusion reactions are thought to result from release of various mediators, such as cytokines. Infusion reactions occurred at any time during a course of treatment with approximately 3% occurring with the first infusion, and approximately 91% occurred during the time of infusion.

KRYSTEXXA should be administered in a healthcare setting by healthcare providers prepared to manage infusion reactions. Patients should be pre-treated with antihistamines and corticosteroids. KRYSTEXXA should be infused slowly over no less than 120 minutes. In the event of an infusion reaction, the infusion should be slowed, or stopped and restarted at a slower rate.

The risk of infusion reaction is higher in patients whose uric acid level increases to above 6 mg/dL, particularly when 2 consecutive levels above 6 mg/dL are observed. Monitor serum uric acid levels prior to infusions and discontinue treatment if levels increase to above 6 mg/dL. Because of the possibility that concomitant use of oral urate-lowering therapy and KRYSTEXXA may potentially blunt the rise of serum uric acid levels, it is recommended that before starting KRYSTEXXA patients discontinue oral urate-lowering medications and not institute therapy with oral urate-lowering agents while taking KRYSTEXXA.

5.3 G6PD Deficiency Associated Hemolysis and Methemoglobinemia

Life threatening hemolytic reactions and methemoglobinemia have been reported with KRYSTEXXA in patients with glucose-6-phosphate dehydrogenase (G6PD) deficiency. Because of the risk of hemolysis and methemoglobinemia, do not administer KRYSTEXXA to patients with G6PD deficiency [see Contraindications (4)]. Screen patients at risk for G6PD deficiency prior to starting KRYSTEXXA. For example, patients of African, Mediterranean (including Southern European and Middle Eastern), and Southern Asian ancestry are at increased risk for G6PD deficiency.

5.4 Gout Flares

In a 52-week, randomized, double-blind trial which evaluated KRYSTEXXA co-administered with methotrexate compared to KRYSTEXXA alone, subjects were administered gout flare prophylaxis similar to that in the pre-marketing, placebo-controlled trials. The percentages of subjects with any flare for the first 3 months were 66% and 69% for the group treated with KRYSTEXXA co-administered with methotrexate and the group treated with KRYSTEXXA alone, respectively. In the group treated with KRYSTEXXA co-administered with methotrexate, the percentages of subjects with any flare for the subsequent 3-month increments of treatment were 27% during Month 6, 8% during Month 9 and 9% during Month 12. In the group treated with KRYSTEXXA alone, the percentages of patients with any flare were 14% during Month 6, 9% during Month 9 and 21% during Month 12.

During pre-marketing, 24-week controlled clinical trials with KRYSTEXXA alone, the frequencies of gout flares were high in all treatment groups, but more so with KRYSTEXXA treatment during the first 3 months of treatment, and decreased in the subsequent 3 months of treatment. The percentages of subjects with any flare for the first 3 months were 74%, 81%, and 51%, for KRYSTEXXA 8 mg every 2 weeks, KRYSTEXXA 8 mg every 4 weeks, and placebo, respectively. The percentages of subjects with any flare for the subsequent 3 months were 41%, 57%, and 67%, for KRYSTEXXA 8 mg every 2 weeks, KRYSTEXXA 8 mg every 4 weeks, and placebo, respectively. Subjects received gout flare prophylaxis with colchicine and/or nonsteroidal anti-inflammatory drugs (NSAIDs) starting at least one week before receiving KRYSTEXXA.

Gout flares may occur after initiation of KRYSTEXXA. An increase in gout flares is frequently observed upon initiation of anti-hyperuricemic therapy, due to changing serum uric acid levels resulting in mobilization of urate from tissue deposits. Gout flare prophylaxis with a non-steroidal anti-inflammatory drug (NSAID) or colchicine is recommended starting at least 1 week before initiation of KRYSTEXXA therapy and lasting at least 6 months, unless medically contraindicated or not tolerated. KRYSTEXXA does not need to be discontinued because of a gout flare. The gout flare should be managed concurrently as appropriate for the individual patient [see Dosage and Administration (2)].

5.5 Congestive Heart Failure

KRYSTEXXA has not been formally studied in patients with congestive heart failure, but some subjects in the pre-marketing, 24-week controlled clinical trials experienced exacerbation of congestive heart failure. Two cases of congestive heart failure exacerbation occurred during the trials in subjects receiving treatment with KRYSTEXXA 8 mg every 2 weeks. No cases were reported in placebo-treated subjects. Four subjects had exacerbations of pre-existing congestive heart failure while receiving KRYSTEXXA 8 mg every 2 weeks during the open-label extension study.

Exercise caution when using KRYSTEXXA in patients who have congestive heart failure and monitor patients closely following infusion.

5.6 Re-treatment with KRYSTEXXA

No controlled trial data are available on the safety and efficacy of re-treatment with KRYSTEXXA after stopping treatment for longer than 4 weeks. Due to the immunogenicity of KRYSTEXXA, patients receiving re-treatment may be at increased risk of anaphylaxis and infusion reactions. Therefore, patients receiving re-treatment after a drug-free interval should be monitored carefully [see Adverse Reactions (6.2)].

6 ADVERSE REACTIONS

The following serious adverse reactions are discussed in greater detail in other sections of the label:

- Anaphylaxis [see Warnings and Precautions (5.1)]
- Infusion Reactions [see Warnings and Precautions (5.2)]
- G6PD Deficiency Associated Hemolysis and Methemoglobinemia [see Warnings and Precautions (5.3)]
- Gout Flares [see Warnings and Precautions (5.4)]
- Congestive Heart Failure [see Warnings and Precautions (5.5)]

6.1 Clinical Trials Experience

Because clinical studies are conducted under widely varying and controlled conditions, adverse reaction rates observed in clinical studies of a drug cannot be directly compared to rates in the clinical studies of another drug, and may not predict the rates observed in a broader patient population in clinical practice.

Co-administration with Methotrexate

A 52-week, randomized, double-blind trial was conducted in adult subjects with chronic gout refractory to conventional therapy to evaluate administration of KRYSTEXXA 8 mg every 2 weeks co-administered with weekly administration of oral methotrexate 15 mg, compared to KRYSTEXXA alone. In this trial, subjects who were able to tolerate two weeks on methotrexate 15 mg were then randomized to receive four additional weeks on either methotrexate 15 mg or matching placebo prior to initiating KRYSTEXXA therapy. A total of 152 subjects were randomized, and of these, 145 subjects completed the 4-week methotrexate run-in period and received KRYSTEXXA (96 subjects received KRYSTEXXA co-administered with methotrexate and 49 received KRYSTEXXA plus placebo) during the treatment period. All subjects received pre-treatment with an oral antihistamine, intravenous corticosteroid and acetaminophen. These subjects were between the ages of 24 and 83 years (average 55 years); 135 subjects were male and 17 and were female; 105 subjects were White/Caucasian, 22 were Black/African American, 14 were Asian, 5 were Native Hawaiian/Other Pacific Islander and 5 identified as Other; 28 were Hispanic or Latino. Common co-morbid conditions among the enrolled subjects included hypertension (63%), osteoarthritis (25%), hyperlipidemia (24%), gastroesophageal reflux disease (22%), obesity (20%), type 2 diabetes (18%) and depression (16%). Subjects with an eGFR <40 mL/min/1.73 m^2 were excluded from this trial.

The most commonly reported adverse reaction during the methotrexate pre-treatment periods was gout flare. The most commonly reported adverse reactions that occurred in ≥ 5% in either treatment group during the KRYSTEXXA co-administered with methotrexate or KRYSTEXXA alone period are provided in Table 1.

Table 1. Adverse Reactions Occurring in 5% or More of Subjects in Either the KRYSTEXXA Co-administered with Methotrexate or KRYSTEXXA Alone Treatment Period
Adverse Reaction | KRYSTEXXA with Methotrexate (N = 96) n (%) | KRYSTEXXA Alone (N = 49) n (%)
Gout flare | 64 (67%) | 35 (71%)
Arthralgia | 13 (14%) | 5 (10%)
COVID-19 | 9 (9%) | 3 (6%)
Nausea | 5 (5%) | 6 (12%)
Fatigue | 5 (5%) | 2 (4%)
Infusion reaction | 4 (4%) [Included one case of anaphylaxis.] | 15 (31%)
Pain in extremity | 1 (1%) | 3 (6%)
Hypertension | 1 (1%) | 3 (6%)
Vomiting | 0 | 4 (8%)

KRYSTEXXA ALONE

The data described below reflect exposure to KRYSTEXXA in subjects with chronic gout refractory to conventional therapy in two replicate randomized, placebo-controlled, double-blind 24-week clinical trials: 85 subjects were treated with KRYSTEXXA 8 mg every 2 weeks; 84 subjects were treated with KRYSTEXXA 8 mg every 4 weeks; and 43 subjects were treated with placebo. These subjects were between the ages of 23 and 89 years (average 55 years); 173 subjects were male and 39 were female; and 143 patients were White/Caucasian, 27 were Black/African American, 24 were Hispanic/Latino and 18 were all other ethnicities. Common co-morbid conditions among the enrolled subjects included hypertension (72%), dyslipidemia (49%), chronic kidney disease (28%), diabetes (24%), coronary artery disease (18%), arrhythmia (16%), and cardiac failure/left ventricular dysfunction (12%).

During the pre-marketing placebo-controlled clinical trials, the most commonly reported adverse reactions that occurred in greater than or equal to 5% of subjects treated with KRYSTEXXA 8 mg every 2 weeks are provided in Table 2.

Table 2. Adverse Reactions Occurring in 5% or More of Subjects Treated with KRYSTEXXA Compared to Placebo
Adverse Reaction | KRYSTEXXA 8 mg every 2 weeks | Placebo
 | (N = 85) n [If the same subject in a given group had more than one occurrence in the same preferred term event category, the subject was counted only once.] (%) | (N = 43) n (%)
Gout flare | 65 (77%) | 35 (81%)
Infusion reaction | 22 (26%) | 2 (5%)
Nausea | 10 (12%) | 1 (2%)
Contusion [Most did not occur on the day of infusion and could be related to other factors (e.g., concomitant medications relevant to contusion or ecchymosis, insulin dependent diabetes mellitus).] or Ecchymosis | 9 (11%) | 2 (5%)
Nasopharyngitis | 6 (7%) | 1 (2%)
Constipation | 5 (6%) | 2 (5%)
Chest Pain | 5 (6%) | 1 (2%)
Anaphylaxis | 4 (5%) | 0 (0%)
Vomiting | 4 (5%) | 1 (2%)

6.2 Postmarketing Experience

The following adverse reactions have been identified during postapproval use of KRYSTEXXA. Because these reactions are reported voluntarily from a population of uncertain size, it is not always possible to reliably estimate their frequency or establish a causal relationship.

General disorders and administration site conditions: asthenia, malaise, peripheral swelling

7 DRUG INTERACTIONS

7.1 Methotrexate

KRYSTEXXA 8 mg every 2 weeks has been studied in patients with chronic gout refractory to conventional therapy taking concomitant oral methotrexate 15 mg weekly [see Clinical Studies (14)]. Co-administration of methotrexate with KRYSTEXXA may increase pegloticase concentration compared to KRYSTEXXA alone [see Clinical Pharmacology (12.3)].

7.2 PEGylated products

Because anti-pegloticase antibodies appear to bind to the PEG portion of the drug, there may be potential for binding with other PEGylated products. The impact of anti-PEG antibodies on patients' responses to other PEG-containing therapeutics is unknown.

8 USE IN SPECIFIC POPULATIONS

8.1 Pregnancy

Risk Summary

There are no adequate and well-controlled studies of KRYSTEXXA in pregnant women.

Based on animal reproduction studies, no structural abnormalities were observed when pegloticase was administered by subcutaneous injection to pregnant rats and rabbits during the period of organogenesis at doses up to 50 and 75 times, respectively, the maximum recommended human dose (MRHD). Decreases in mean fetal and pup body weights were observed at approximately 50 and 75 times the MRHD, respectively [see Data].

All pregnancies have a background risk of birth defect, loss or other adverse outcomes. In the US general population, the estimated background risk of major birth defects and miscarriage in clinical recognized pregnancies is 2% to 4% and 15% to 20%, respectively.

Data

Animal Data

In 2 separate embryo-fetal developmental studies, pregnant rats and rabbits received pegloticase during the period of organogenesis at doses up to approximately 50 and 75 times the MRHD, respectively (on a mg/m^2 basis at maternal doses up to 40 and 30 mg/kg twice weekly, in rats and rabbits, respectively). No evidence of structural abnormalities was observed in rats or rabbits. However, decreases in mean fetal and pup body weights were observed at approximately 50 and 75 times the MRHD in rats and rabbits, respectively (on a mg/m^2 basis at maternal doses up to 40 and 30 mg/kg every other day, in rats and rabbits, respectively). No effects on mean fetal body weights were observed at approximately 10 and 25 times the MRHD in rats and rabbits, respectively (on a mg/m^2 basis at maternal doses up to 10 mg/kg twice weekly in both species).

8.2 Lactation

Risk Summary

It is not known whether this drug is excreted in human milk. Therefore, KRYSTEXXA should not be used when breastfeeding unless the clear benefit to the mother can overcome the unknown risk to the newborn/infant.

8.4 Pediatric Use

The safety and effectiveness of KRYSTEXXA in pediatric patients less than 18 years of age have not been established.

8.5 Geriatric Use

Of the total number of patients treated with KRYSTEXXA 8 mg every 2 weeks in the controlled studies, 34% (29 of 85) were 65 years of age and older and 12% (10 of 85) were 75 years of age and older. No overall differences in safety or effectiveness were observed between older and younger patients, but greater sensitivity of some older individuals cannot be ruled out. No dose adjustment is needed for patients 65 years of age and older.

8.6 Renal Impairment

No dose adjustment is required for patients with renal impairment. In a 52-week, randomized, double-blind trial which evaluated KRYSTEXXA co-administered with methotrexate compared to KRYSTEXXA alone, 85% of patients had chronic kidney disease based on estimated glomerular filtration rate (eGFR) of ≥ 40 to < 90 mL/min/1.73m^2 at baseline. In the pre-marketing 24-week controlled clinical trials with KRYSTEXXA alone, a total of 32% (27 of 85) of subjects treated with KRYSTEXXA 8 mg every 2 weeks had a creatinine clearance of ≤62.5 mL/min. No overall differences in efficacy were observed.

10 OVERDOSAGE

No reports of overdosage with KRYSTEXXA have been reported. The maximum dose that has been administered as a single intravenous dose is 12 mg as uricase protein.

Patients suspected of receiving an overdose should be monitored, and general supportive measures should be initiated as no specific antidote has been identified.

11 DESCRIPTION

Pegloticase is a uric acid specific enzyme which is a PEGylated product that consists of recombinant modified mammalian urate oxidase (uricase) produced by a genetically modified strain of Escherichia coli. Uricase is covalently conjugated to monomethoxypoly (ethylene glycol) [mPEG] (10 kDa molecular weight). The cDNA coding for uricase is based on mammalian sequences. Each uricase subunit has a molecular weight of approximately 34 kDa per subunit. The average molecular weight of pegloticase (tetrameric enzyme conjugated to mPEG) is approximately 540 kDa.

Ready-to-Use KRYSTEXXA (pegloticase) injection 8 mg/50 mL (0.16 mg/mL) single-dose vial is supplied as a sterile, preservative-free, clear and colorless solution intended for intravenous infusion and does not require further dilution. Each 8 mg/50 mL (0.16 mg/mL) single-dose vial contains 50 mL of deliverable volume including 8 mg of uricase protein (conjugated to 24 mg of 10 kDa mPEG), Disodium Hydrogen Phosphate Heptahydrate (109 mg), Sodium Chloride (438.5 mg), Sodium Dihydrogen Phosphate Monohydrate (13mg), and Water for Injection to deliver 8 mg of pegloticase (as uricase protein).

To-be-Diluted KRYSTEXXA (pegloticase) injection 8 mg/mL single-dose vial is supplied as a sterile, preservative-free, clear and colorless solution intended for intravenous infusion after dilution. KRYSTEXXA (pegloticase) concentrations are expressed as concentrations of uricase protein. Each 8 mg/mL single-dose vial contains 1 mL of deliverable volume including 8 mg of uricase protein (conjugated to 24 mg of 10 kDa mPEG), Disodium Hydrogen Phosphate Dihydrate (2.18 mg), Sodium Chloride (8.77 mg), Sodium Dihydrogen Phosphate Dihydrate (0.43 mg), and Water for Injection to deliver 8 mg of pegloticase (as uricase protein).

12 CLINICAL PHARMACOLOGY

12.1 Mechanism of Action

KRYSTEXXA is a uric acid specific enzyme which is a recombinant uricase and achieves its therapeutic effect by catalyzing the oxidation of uric acid to allantoin, thereby lowering serum uric acid. Allantoin is an inert and water-soluble purine metabolite; it is readily eliminated, primarily by renal excretion.

12.2 Pharmacodynamics

Approximately 24 hours following the first dose of KRYSTEXXA, mean plasma uric acid levels for subjects in the KRYSTEXXA groups were 0.7 mg/dL for the KRYSTEXXA 8 mg every 2 weeks group. In comparison, the mean plasma uric acid level for the placebo group was 8.2 mg/dL.

In a single-dose, dose-ranging trial, following 1-hour intravenous infusions of 0.5, 1, 2, 4, 8 or 12 mg of pegloticase in 24 patients with symptomatic gout (n = 4 subjects/dose group), plasma uric acid decreased with increasing pegloticase dose or concentrations. The duration of suppression of plasma uric acid appeared to be positively associated with pegloticase dose. Sustained decrease in plasma uric acid below the solubility concentration of 6 mg/dL for more than 300 hours was observed with doses of 8 mg and 12 mg.

12.3 Pharmacokinetics

Pegloticase levels were determined in serum based on measurements of uricase enzyme activity.

Following single intravenous infusions of 0.5 mg to 12 mg pegloticase in 23 patients with symptomatic gout, maximum serum concentrations of pegloticase increased in proportion to the dose administered.

The population pharmacokinetic analysis showed that age, sex, weight, and creatinine clearance did not influence the pharmacokinetics of pegloticase. Significant covariates impacting pegloticase pharmacokinetics were body surface area and anti-pegloticase antibodies.

Special Populations

Pediatric Patients

The pharmacokinetics of pegloticase has not been studied in children and adolescents.

Patients with Renal or Hepatic Impairment

No formal studies were conducted to examine the effects of either renal or hepatic impairment on pegloticase pharmacokinetics. eGFR was not a significant covariate on pegloticase pharmacokinetics.

Drug Interactions

Co-administration of methotrexate with KRYSTEXXA decreased anti-pegloticase antibody incidence rate and titers compared to KRYSTEXXA alone, therefore increased pegloticase exposure levels. In patients with chronic gout refractory to conventional therapy receiving KRYSTEXXA 8 mg every 2 weeks co-administered with weekly administration of oral methotrexate 15 mg, higher steady-state peak and trough concentrations (2.65 µg/mL and 1.13 µg/mL, respectively) of pegloticase were observed compared to when KRYSTEXXA is given alone (steady-state peak and trough concentrations at 2.13 µg/mL and 0.59 µg/mL, respectively).

12.6 Immunogenicity

As with all therapeutic proteins, there is a potential for immunogenicity. The observed incidence of antibody positivity in an assay is highly dependent on several factors including assay sensitivity and specificity and assay methodology, sample handling, timing of sample collection, concomitant medications, and underlying disease. For these reasons, the comparison of the incidence of antibodies to pegloticase with the incidence of antibodies to other products may be misleading.

In a 52-week, randomized, double-blind trial which evaluated KRYSTEXXA co-administered with methotrexate compared to KRYSTEXXA alone, approximately 26% of patients had pre-existing antibodies to pegloticase. Patients with an increase in titer from baseline or who were negative at baseline and developed an anti-pegloticase response at one or more post dose time points was 30% and 51%, for the KRYSTEXXA co-administered with methotrexate and KRYSTEXXA alone treatment groups, respectively. Patients with higher antibody titers were more likely to have faster clearance and lower efficacy.

During pre-marketing 24-week controlled clinical trials with KRYSTEXXA alone, anti-pegloticase antibodies developed in 92% of patients treated with KRYSTEXXA every 2 weeks, and 28% for placebo. Anti-PEG antibodies were also detected in 42% of patients treated with KRYSTEXXA. High anti-pegloticase antibody titer was associated with a failure to maintain pegloticase-induced normalization of uric acid. The impact of anti-PEG antibodies on patients' responses to other PEG-containing therapeutics is unknown.

There was a higher incidence of infusion reactions in patients with high anti-pegloticase antibody titer: 53% (16 of 30) in the KRYSTEXXA every 2 weeks group compared to 6% in patients who had undetectable or low antibody titers.

13 NONCLINICAL TOXICOLOGY

13.1 Carcinogenesis, Mutagenesis, Impairment of Fertility

Long-term animal studies have not been performed to evaluate the carcinogenic potential of pegloticase.

The genotoxic potential of pegloticase has not been evaluated.

There was no evidence of impairment on fertility at pegloticase doses up to 40 mg/kg (approximately 50 times the MRHD on mg/m^2 basis) every other day in rats.

13.2 Animal Toxicology and/or Pharmacology

Pegloticase at similar to and higher than the maximum recommended human dose (MRHD) on a plasma Area Under Curve (AUC) basis [at intravenous (IV) doses of ≥ 0.4 mg/kg in dogs] caused cytoplasmic vacuoles in multiple organs, and edema and histiocyte infiltration in the aortic outflow tract in dogs. Organs with cytoplasmic vacuoles included the spleen, adrenal gland, liver, heart, duodenum, and jejunum. Vacuoles in the spleen, adrenal glands, and heart persisted after a 1-year recovery period at pegloticase doses (≥ 1.5 mg/kg in dogs) approximately 5 times the MRHD, but were absent at a dose similar to the MRHD. Vacuoles in the liver, duodenum, and jejunum persisted after a 3-month recovery period at a pegloticase dose (10 mg/kg in dogs) approximately 30 times the MRHD, but were absent at doses (≤ 1.5 mg/kg) approximately 5 times and similar to the MRHD. The edema and histiocyte infiltration in the aortic outflow tract was absent after recovery periods of 6 and 12 months, respectively.

Vacuoles in the spleen, liver, duodenum, and jejunum were within macrophages and most likely represented phagocytic removal of pegloticase from the circulation. However, the vacuolated cells in the heart and adrenal gland did not stain as macrophages. In the aortic outflow tract of the heart, vacuoles were in the cytoplasm of endothelial cells in the intimal lining of the aorta. In the adrenal gland, vacuoles were located within cortical cells in the zona reticularis and zona fasciculata. The clinical significance of these findings and the functional consequences are unknown.

14 CLINICAL STUDIES

Co-administration with Methotrexate

A 52-week, randomized, double-blind trial was conducted in adult subjects with chronic gout refractory to conventional therapy, to evaluate administration of KRYSTEXXA 8 mg every 2 weeks co-administered with weekly administration of methotrexate 15 mg, compared to KRYSTEXXA alone: Trial 1 (NCT03994731). In this trial, patients were naïve to KRYSTEXXA therapy. Subjects who were able to tolerate two weeks on oral methotrexate 15 mg were then randomized to receive four additional weeks on either methotrexate 15 mg or matching placebo prior to initiating KRYSTEXXA therapy in a 2:1 ratio. Subjects were pre-treated with a standardized infusion reaction prophylaxis regimen consisting of an oral fexofenadine, acetaminophen and intravenous methylprednisolone prior to each KRYSTEXXA infusion. Methotrexate or placebo was continued weekly throughout the KRYSTEXXA treatment period with daily oral folic acid in order to evaluate the immunomodulatory effect of methotrexate to attenuate development of anti-drug antibodies.

Entry criteria for subjects to be eligible for this trial were: baseline serum uric acid ≥7 mg/dL and inability to maintain serum uric acid <6 mg/dL on other urate-lowering therapy, intolerable side effects associated with current urate-lowering therapy, and/or presence of clinically evident tophaceous deposits.

The primary endpoint was the proportion of Month 6 responders, where a responder was defined as achieving and maintaining serum uric acid less than 6 mg/dL for at least 80% of the time during Month 6. The proportion of Month 12 responders was a key secondary endpoint. A significantly greater proportion of patients receiving KRYSTEXXA co-administered with methotrexate compared to KRYSTEXXA alone achieved both the primary and secondary endpoints (see Table 3).

Table 3. Serum Uric Acid < 6 mg/dL for at Least 80% of the Time During Month 6 and During Month 12 in Subjects Administered KRYSTEXXA Co-administered with Methotrexate
 | Treatment Group
Trial 1 | KRYSTEXXA with Methotrexate (N = 100) | KRYSTEXXA Alone (N = 52)
Number, % of Patients Who Met Response Criteria During Month 6 | 71 (71%) | 20 (39%)
Difference [Difference and its corresponding 95% confidence interval (CI) based on a weighted average of the difference within each randomization stratum (tophi presence, no tophi presence) using Cochran-Mantel-Haenszel (CMH) weights.] (95% Confidence Interval) | 32% (16%, 48%)
P-Value | <0.0001
Number, % of Patients Who Met Response Criteria During Month 12 | 60 (60%) | 16 (31%)
Difference (95% Confidence Interval) | 29% (13%, 45%)
P-Value | 0.0003

The effect of KRYSTEXXA co-administered with methotrexate and KRYSTEXXA alone on tophi was assessed using standardized digital photography, image analysis and Central Readers blinded to treatment assignment. Approximately 53.3% (81/152) of randomized subjects had tophi at baseline (Week-6) that were confirmed by digital photography. Of those, 54% (28/52) in the KRYSTEXXA co-administered with methotrexate group and 31% (9/29) in the KRYSTEXXA alone group achieved a complete response at Month 12 (defined as 100% resolution of at least one target tophus, no new tophi appear and no single tophus showing progression). The difference between the two treatment groups was statistically significant (22.8%, 95% CI: 1.2%, 44.4%).

KRYSTEXXA ALONE

The efficacy of KRYSTEXXA was studied in adult patients with chronic gout refractory to conventional therapy in two replicate, multicenter, randomized, double-blind, placebo-controlled studies of six months duration: Trial 2 and Trial 3. Patients were randomized to receive KRYSTEXXA 8 mg every 2 weeks or every 4 weeks or placebo in a 2:2:1 ratio.

Studies were stratified for the presence of tophi. Seventy-one percent (71%) of subjects had baseline tophi. All subjects were prophylaxed with an oral antihistamine, intravenous corticosteroid and acetaminophen. Subjects also received prophylaxis for gout flares with non-steroidal anti-inflammatory drugs (NSAIDs) or colchicine, or both, beginning at least one week before KRYSTEXXA treatment unless medically contraindicated or not tolerated. Subjects who completed the randomized clinical trials were eligible to enroll in a 2-year open label extension study.

Entry criteria for subjects to be eligible for the trials were: baseline serum uric acid of at least 8 mg/dL; had symptomatic gout with at least 3 gout flares in the previous 18 months or at least 1 gout tophus or gouty arthritis; and had a self-reported medical contraindication to allopurinol or medical history of failure to normalize uric acid (to less than 6 mg/dL) with at least 3 months of allopurinol treatment at the maximum medically appropriate dose.

The mean age of study subjects was 55 years (23-89); 82% were male, mean body mass index (BMI) was 33 kg/m^2, mean duration of gout was 15 years, and mean baseline serum uric acid was 10 mg/dL.

To assess the efficacy of KRYSTEXXA in lowering uric acid, the primary endpoint in both trials was the proportion of subjects who achieved plasma uric acid (PUA) less than 6 mg/dL for at least 80% of the time during Month 3 and Month 6. As shown in Table 4, a greater proportion of subjects treated with KRYSTEXXA every 2 weeks achieved urate-lowering to below 6 mg/dL than subjects receiving placebo. Although the 4-week regimen also demonstrated efficacy for the primary endpoint, this regimen was associated with increased frequency of anaphylaxis and infusion reactions and less efficacy with respect to tophi.

Table 4. Plasma Uric Acid < 6 mg/dL for at Least 80% of the Time During Months 3 and 6
Treatment Group | N | Number (%) of Subjects Who Met Response Criteria | 95% Confidence Interval [95% confidence interval for differences in responder rate between pegloticase group vs. placebo.] | P-Value [P-value using Fisher's exact test to compare pegloticase group vs. placebo.]
Trial 2
KRYSTEXXA 8 mg every 2 weeks | 43 | 20 (47%) | [32%, 61%] | <0.001
KRYSTEXXA 8 mg every 4 weeks | 41 | 8 (20%) | [7%, 32%] | 0.044
Placebo | 20 | 0 (0%)
Trial 3
KRYSTEXXA 8 mg every 2 weeks | 42 | 16 (38%) | [23%, 53%] | <0.001
KRYSTEXXA 8 mg every 4 weeks | 43 | 21 (49%) | [34%, 64%] | <0.001
Placebo | 23 | 0 (0%)
Note: Based on post-hoc analyses of the clinical trial data, if KRYSTEXXA had been stopped when a patient's uric acid level rose to greater than 6 mg/dL on a single occasion, the incidence of infusion reactions would have been reduced by approximately 67%, but the success rates for the primary efficacy endpoint would have been reduced by approximately 20%. If KRYSTEXXA had been stopped after 2 consecutive uric acid levels greater than 6 mg/dL, the incidence of infusion reactions would have been half, and there would have been little change in the efficacy outcome.

The effect of treatment on tophi was a secondary efficacy endpoint and was assessed using standardized digital photography, image analysis, and a Central Reader blinded to treatment assignment. Approximately 70% of subjects had tophi at baseline. A pooled analysis of data from Trial 2 and Trial 3 (NCT00325195) was performed as pre-specified in the protocols. At Month 6, the percentage of subjects who achieved a complete response (defined as 100% resolution of at least one target tophus, no new tophi appear and no single tophus showing progression) was 45%, 26%, and 8%, with KRYSTEXXA 8 mg every 2 weeks, KRYSTEXXA 8 mg every 4 weeks, and placebo, respectively. The difference between KRYSTEXXA and placebo was statistically significant for the every 2-week dosing regimen, but not for the every 4-week dosing regimen.

16 HOW SUPPLIED/STORAGE AND HANDLING

How Supplied

KRYSTEXXA (pegloticase) injection is supplied as a sterile, clear and colorless solution containing 8 mg of pegloticase as follows for intravenous infusion:

- One Ready-to-Use 8 mg/50 mL (0.16 mg/mL) single-dose vial (NDC 75987-058-01)
- One To-be-Diluted 8 mg/mL single-dose vial (NDC 75987-080-10)

Storage and Handling

Before the preparation for use, KRYSTEXXA must be stored in the carton and maintained at all times under refrigeration between 2°C to 8°C (36°F to 46°F). Protect from light. Do not shake or freeze.

Do not use beyond the expiration date stamped.

17 PATIENT COUNSELING INFORMATION

Advise patients to read the FDA-approved patient labeling (Medication Guide).

Anaphylaxis and Infusion Reactions

- Anaphylaxis and infusion reactions can occur at any infusion while on therapy. Counsel patients on the importance of adhering to any prescribed medications, to help prevent or lessen the severity of these reactions.
- Educate patients on the signs and symptoms of anaphylaxis, including wheezing, peri-oral or lingual edema, hemodynamic instability, and rash or urticaria, nausea or vomiting.
- Educate patients on the most common signs and symptoms of an infusion reaction, including urticaria (skin rash), erythema (redness of the skin), dyspnea (difficulty breathing), flushing, chest discomfort, chest pain, and rash.
- Advise patients to seek medical care immediately if they experience any symptoms of an allergic reaction during or at any time after the infusion of KRYSTEXXA [see Warnings and Precautions (5.1, 5.2), Adverse Reactions (6.1)].
- Advise patients to discontinue any oral urate-lowering agents before starting on KRYSTEXXA and not to take any oral urate-lowering agents while on KRYSTEXXA.

Glucose-6-phosphate dehydrogenase (G6PD) Deficiency

Inform patients not to take KRYSTEXXA if they have a condition known as G6PD deficiency. Explain to patients that G6PD deficiency is more frequently found in individuals of African, Mediterranean, or Southern Asian ancestry and that they may be tested to determine if they have G6PD deficiency, unless already known [see Contraindications (4), Warnings and Precautions (5.3)].

Gout Flares

Explain to patients that gout flares may initially increase when starting treatment with KRYSTEXXA, and that medications to help reduce flares may need to be taken regularly for the first few months after KRYSTEXXA is started [see Warnings and Precautions (5.4), Adverse Reactions (6.1)]. Advise patients that they should not stop KRYSTEXXA therapy if they have a flare.

AMGEN

KRYSTEXXA® (pegloticase)

Manufactured by:
Horizon Therapeutics Ireland DAC
Dublin, Ireland
US License Number 2022

Patent: https://pat.amgen.com/krystexxa/
© 2025 Amgen Inc. All rights reserved.

1xxxxx – v6

Medication Guide
KRYSTEXXA® (kris-TEX-a)
(pegloticase)
injection, for intravenous use

Read this Medication Guide before you start receiving KRYSTEXXA and before each treatment. There may be new information. This Medication Guide does not take the place of talking with your doctor about your medical condition or treatment. Talk to your doctor if you have any questions about your treatment with KRYSTEXXA.

What is the most important information I should know about KRYSTEXXA?
Serious allergic reactions may happen in some people who receive KRYSTEXXA. These allergic reactions can be life threatening and usually happen within 2 hours of the infusion.
KRYSTEXXA should be given to you by a doctor or nurse in a healthcare setting where serious allergic reactions can be treated. Your doctor or nurse should watch you for any signs of a serious allergic reaction during and after your treatment with KRYSTEXXA.
Tell your doctor or nurse right away if you have any of these symptoms during or after your treatment with KRYSTEXXA:

- wheezing, shortness of breath, cough, chest tightness, chest pain, or trouble breathing
- dizziness, fainting, fast or weak heartbeat or feeling nervous
- reddening of the face, itching, hives, or feeling warm
- swelling of the throat or tongue, throat tightness, hoarse voice or trouble swallowing

What is KRYSTEXXA?

- KRYSTEXXA is a prescription medicine used in adults to help reduce the signs and symptoms of gout that are not controlled by other treatments.
- People with gout have too much uric acid in their bodies. Uric acid crystals collect in joints, kidneys, and other organs. This may cause pain, redness and swelling (inflammation). KRYSTEXXA works to lower blood levels of uric acid.
- KRYSTEXXA is not for use in people with too much uric acid in their bodies who do not have symptoms (asymptomatic hyperuricemia).

It is not known if KRYSTEXXA is safe and effective in children under 18 years of age.

Who should not receive KRYSTEXXA?
Do not receive KRYSTEXXA if you:

- have a rare blood problem called glucose 6-phosphate dehydrogenase (G6PD) deficiency or favism. Your doctor may test you for G6PD before you start KRYSTEXXA.
- have had a serious allergic reaction to KRYSTEXXA or any of its ingredients. See the end of this Medication Guide for a complete list of ingredients in KRYSTEXXA.

What should I tell my doctor before receiving treatment with KRYSTEXXA?
Before you receive KRYSTEXXA, tell your doctor about all of your medical conditions, including if you:

- ever had any heart problems or high blood pressure.
- are pregnant or plan to become pregnant. It is not known if KRYSTEXXA will harm your unborn baby. Talk to your doctor if you are pregnant or plan to become pregnant.
- are breastfeeding or plan to breastfeed. It is not known if KRYSTEXXA passes into your breast milk. You and your doctor should decide if you will receive KRYSTEXXA or breastfeed.

Tell your doctor about all the medicines you take, including prescription and over-the-counter medicines, vitamins, and herbal supplements. Do not take any other uric acid lowering drug, such as allopurinol, febuxostat (Uloric) or probenecid, while receiving KRYSTEXXA.
Know the medicines you take. Keep a list of your medicines and show them to your doctor and pharmacist when you get a new medicine.

How will I receive KRYSTEXXA?

- KRYSTEXXA is recommended to be given with another prescription medicine called methotrexate.
  KRYSTEXXA may also be used alone. You and your doctor will decide the treatment that is right for you.
- Your doctor may give you medicine before your treatment of KRYSTEXXA to help reduce your risk of getting gout flares or an allergic reaction. Take these medicines as directed by your doctor or nurse.
- You will receive KRYSTEXXA through a needle in your vein (intravenous infusion).
- Your treatment will take about 2 hours or sometimes longer. A doctor or nurse will give you the treatment.
- You will receive KRYSTEXXA every 2 weeks.
- If you have side effects, your doctor may stop or slow the infusion and may give you medicine to help the side effects.
- A doctor or nurse will watch you for side effects while you receive KRYSTEXXA and for some time afterwards.
- Your doctor may stop your KRYSTEXXA if your uric acid levels do not become normal and stay controlled or you have certain side effects.
- Your gout flares may increase in the first 3 months when you start receiving KRYSTEXXA. Do not stop receiving KRYSTEXXA even if you have a flare as the amount of flares will decrease after 3 months of treatment. Your doctor may give you other medicines to help reduce your gout flares for the first few months after starting KRYSTEXXA.

What are the possible side effects of KRYSTEXXA?
KRYSTEXXA may cause serious side effects.
See "What is the most important information I should know about KRYSTEXXA?"
The most common side effects of KRYSTEXXA when given together with methotrexate include:

- gout flares
- joint pain
- coronavirus disease 2019 (COVID-19)
- nausea
- fatigue

The most common side effects of KRYSTEXXA include:

- gout flares
- allergic reactions (including infusion reactions). See "What is the most important information I should know about KRYSTEXXA?"
- nausea
- bruising
- sore throat
- constipation
- chest pain
- coronavirus disease 2019 (COVID-19)
- vomiting

Tell your doctor if you have any side effect that bothers you or that does not go away.
These are not all of the side effects of KRYSTEXXA. For more information, ask your doctor or pharmacist.
Call your doctor for medical advice about side effects. You may report side effects to FDA at 1-800-FDA-1088. You may also report side effects to Amgen Inc. at 1-800-77-AMGEN (1-800-772-6436).

General information about the safe and effective use of KRYSTEXXA.
Medicines are sometimes prescribed for purposes other than those listed in a Medication Guide. This Medication Guide summarizes the most important information about KRYSTEXXA. If you would like more information, talk with your doctor. You can ask your pharmacist or doctor for information about KRYSTEXXA that is written for health professionals.
For more information, go to www.KRYSTEXXA.com or call 1-866-479-6742.

What are the ingredients in KRYSTEXXA?
Active ingredient: pegloticase
Inactive ingredients:
Ready-to-Use KRYSTEXXA 8 mg/50 mL (0.16 mg/mL) single-dose vial: disodium hydrogen phosphate heptahydrate, sodium chloride, sodium dihydrogen phosphate monohydrate, and water for injection.
To-be-Diluted KRYSTEXXA 8 mg/mL single-dose vial: disodium hydrogen phosphate dihydrate, sodium chloride, sodium dihydrogen phosphate dihydrate, and water for injection.
AMGEN
Manufactured by:
Horizon Therapeutics Ireland DAC
Dublin, Ireland
U.S. License Number 2022
© 2025 Amgen Inc. All rights reserved. V7

This Medication Guide has been approved by the U.S. Food and Drug Administration.

Revised: 8/2025

PRINCIPAL DISPLAY PANEL - 8 mg/mL Vial Carton

NDC-75987-080-10

KRYSTEXXA®
pegloticase

Injection

8 mg/mL

For Intravenous Infusion

Single-dose vial. Discard unused portion.
Must Be Diluted Prior to Administration.

Dispense the enclosed
Medication Guide
to each patient.

Rx Only

PRINCIPAL DISPLAY PANEL - 50 mL Vial Carton

NDC-75987-058-01

KRYSTEXXA®
pegloticase

Injection

8 mg per 50 mL (0.16 mg/mL)

For Intravenous Infusion

Ready-to-Use Presentation and
does NOT require further dilution.

Contains 1 Single-dose vial. Discard unused portion.

Dispense the enclosed
Medication Guide
to each patient.

Rx Only

AMGEN